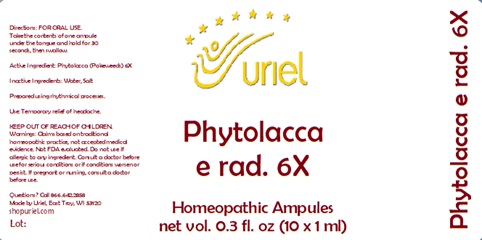 DRUG LABEL: Phytolacca e rad 6X
NDC: 48951-8431 | Form: LIQUID
Manufacturer: Uriel Pharmacy Inc.
Category: homeopathic | Type: HUMAN OTC DRUG LABEL
Date: 20241217

ACTIVE INGREDIENTS: PHYTOLACCA AMERICANA ROOT 6 [hp_X]/1 mL
INACTIVE INGREDIENTS: WATER; SODIUM CHLORIDE

Phytolacca e rad 6X

INDICATIONS AND USAGE

Directions: FOR ORAL USE.

DOSAGE AND ADMINISTRATION

Take the contents of one ampule under the tongue and hold for 30 seconds, then swallow.

Active Ingredient: Phytolacca (Pokeweeds) 6X

Inactive Ingredients: Water, Salt

Prepared using rhythmical processes.

PURPOSE

Use: Temporary relief of headache.

KEEP OUT OF REACH OF CHILDREN.

WARNINGS

Warnings: Claims based on traditional homeopathic practice, not accepted medical evidence. Not FDA evaluated. Do not use if allergic to any ingredient. Consult a doctor before use for serious conditions or if conditions worsen or persist. If pregnant or nursing, consult a doctor before use.

QUESTIONS

Questions? Call 866.642.2858 Made by Uriel, East Troy, WI 53120 shopuriel.com Lot: